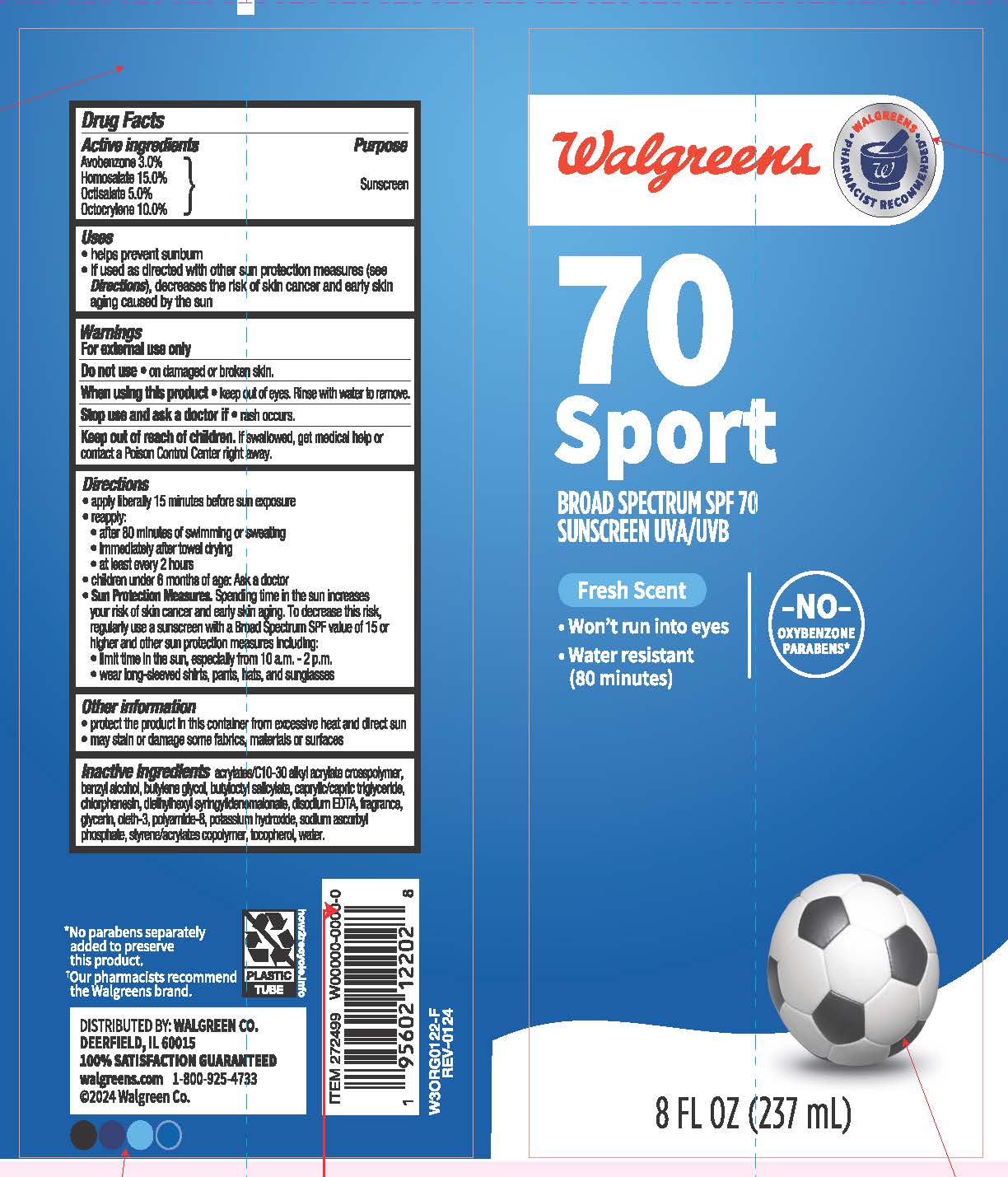 DRUG LABEL: Walgreens 70 Sport Sunscreen
NDC: 0363-1362 | Form: LOTION
Manufacturer: WALGREEN COMPANY
Category: otc | Type: HUMAN OTC DRUG LABEL
Date: 20260128

ACTIVE INGREDIENTS: HOMOSALATE 150 mg/1 mL; AVOBENZONE 30 mg/1 mL; OCTOCRYLENE 100 mg/1 mL; OCTISALATE 50 mg/1 mL
INACTIVE INGREDIENTS: CAPRYLIC/CAPRIC TRIGLYCERIDE; CARBOMER COPOLYMER TYPE A; EDETATE DISODIUM; WATER; GLYCERIN; SODIUM ASCORBYL PHOSPHATE; .ALPHA.-TOCOPHEROL, DL-; BUTYLENE GLYCOL; OLETH-3; POLYAMIDE-8 (4500 MW); BUTYLOCTYL SALICYLATE; DIETHYLHEXYL SYRINGYLIDENEMALONATE; POTASSIUM HYDROXIDE; BENZYL ALCOHOL; CHLORPHENESIN

Walgreens SPF 70 Sport Sunscreen

Active ingredients

Avobenzone 3.0%, Homosalate 15.0%, Octisalate 5.0%, Octocrylene 10.0%

Purpose

Sunscreen

Uses

▪ helps prevent sunburn

▪ if used as directed with other sun protection measures (see Directions), decreases the risk of skin cancer and early skin aging caused by the sun.

Warnings

For external use only

Do not use

- on damaged or broken skin.

When using this product

- keep out of eyes. Rinse with water to remove.

Stop use and ask a doctor if

- rash occurs.

Keep out of reach of children.

▪ If swallowed, get medical help or contact a Poison Control Center right away.

Directions

- apply liberally 15 minutes before sun exposure
- reapply:
- after 80 minutes of swimming or sweating
- immediately after towel drying
- at least every 2 hours
- children under 6 months of age: Ask a doctor
- Sun Protection Measures. Spending time in the sun increases your risk of skin cancer and early skin aging. To decrease this risk, regularly use a sunscreen with a Broad Spectrum SPF value of 15 or higher and other sun protection measures including:
- limit time in the sun, especially from 10 a.m. - 2 p.m.
- wear long-sleeved shirts, pants, hats, and sunglasses

Other information

- protect the product in this container from excessive heat and direct sun
- may stain or damage some fabrics, materials or surfaces

Inactive ingredients

acrylates/C10-30 alkyl acrylate crosspolymer, benzyl alcohol, butylene glycol, butyloctyl salicylate, caprylic/capric triglyceride, chlorphenesin, diethylhexyl syringylidenemalonate, disodium EDTA, fragrance, glycerin, oleth-3, polyamide-8, potassium hydroxide, sodium ascorbyl phosphate, styrene/acrylates copolymer, tocopherol, water.